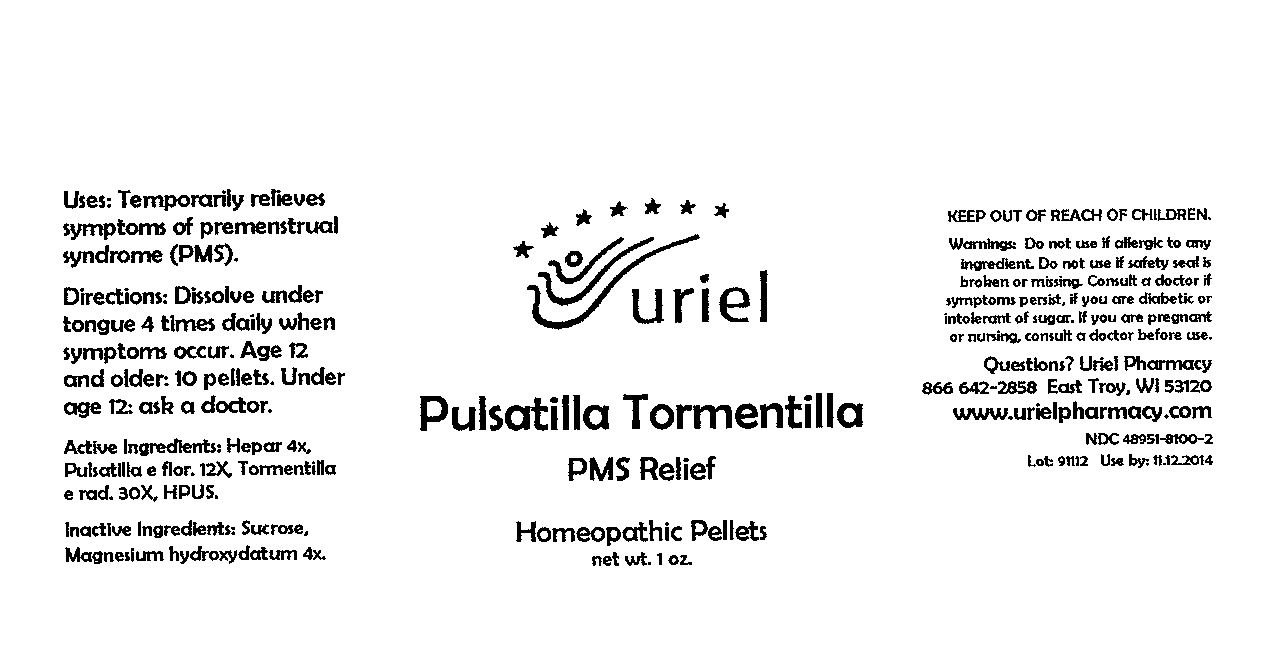 DRUG LABEL: Pulsatilla Tormentilla PMS Relief
NDC: 48951-8100 | Form: PELLET
Manufacturer: Uriel Pharmacy Inc
Category: homeopathic | Type: HUMAN OTC DRUG LABEL
Date: 20091211

ACTIVE INGREDIENTS: MAMMAL LIVER 4 [hp_X]/1 1; PULSATILLA VULGARIS 12 [hp_X]/1 1; ACHILLEA MILLEFOLIUM 30 [hp_X]/1 1
INACTIVE INGREDIENTS: SUCROSE

Pulsatilla Tormentilla PMS Relief Pellets - 1 oz.

Purpose

Uses: Temporarily relieves symptoms of premenstrual syndrome (PMS).

Dosage & Administration

Directions: Dissolve under tongue 4 times daily when symptoms occur. Age 12 and older: 10 pellets. Under age 12: ask a doctor.

OTC-Active Ingredient

Active Ingredients: Hepar 4x, Pulsatilla e flor. 12X, Tormentilla e rad. 30X, HPUS.

Inactive Ingredient

Inactive Ingredients: Sucrose, Magnesium hydroxydatum 4x.

Keep out of reach of children

Do not use section

Warnings:Do not use if allergic to any ingredient. Do not use if safety seal is broken or missing.

Ask doctor section

Consult a doctor if symptoms persist, if you are diabetic or intolerant of sugar.

Pregnancy or breast feeding section

If you are pregnant or nursing, consult a doctor before use.

Questions section

Questions? Uriel Pharmacy

866 642-2858 East Troy, WI 53120

www.urielpharmacy.com

NDC 48951-8100-2

Principal Display Panel

Pulsatilla Tormentilla

PMS Relief

Homeopathic Pellets

net wt. 1 oz.